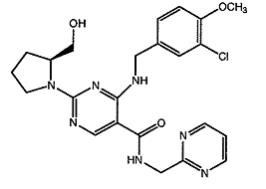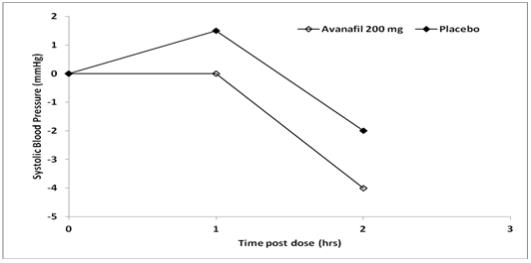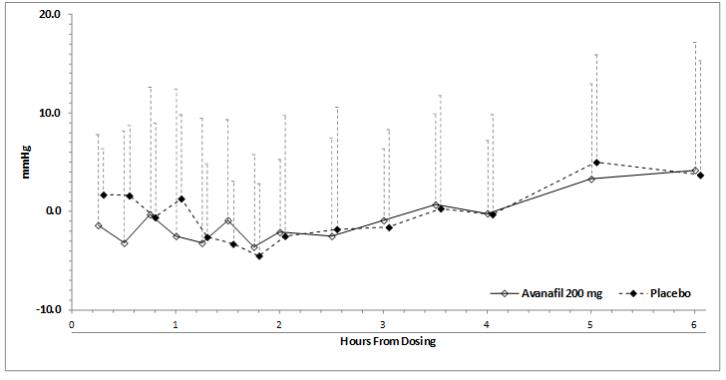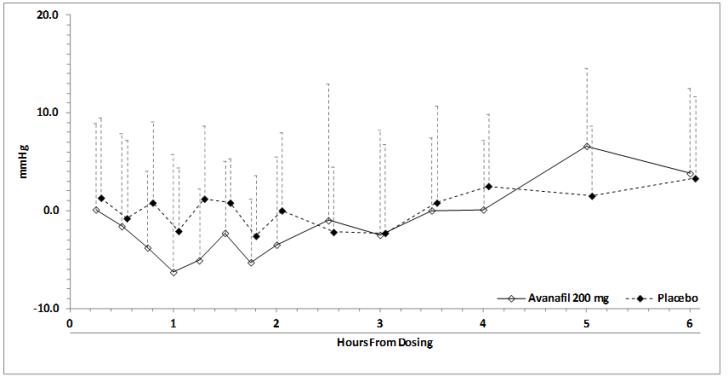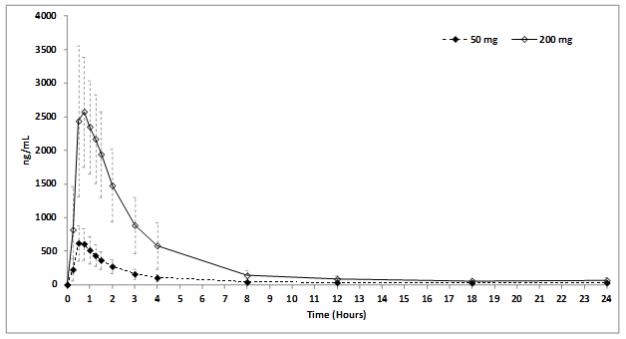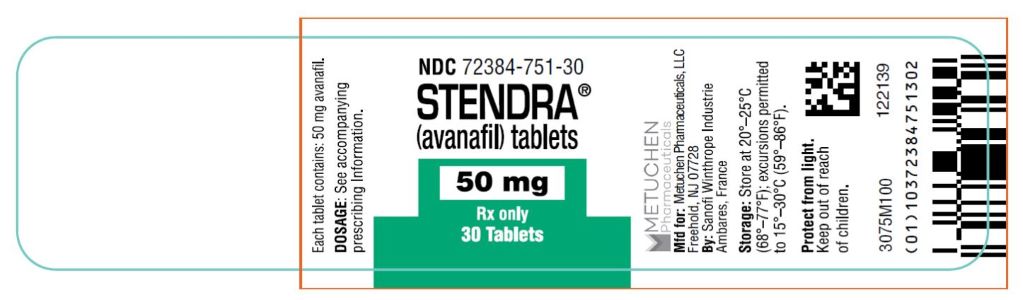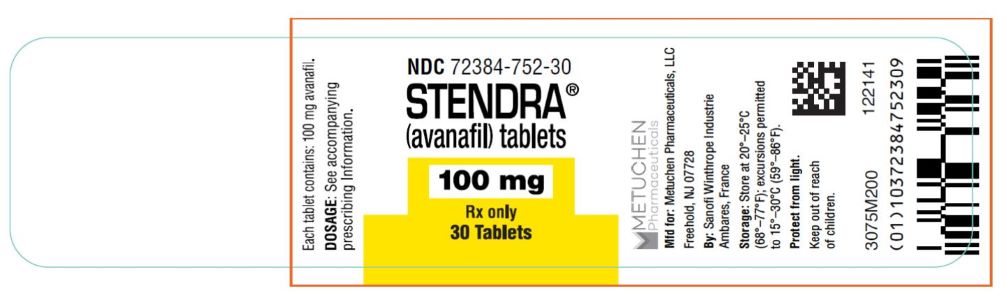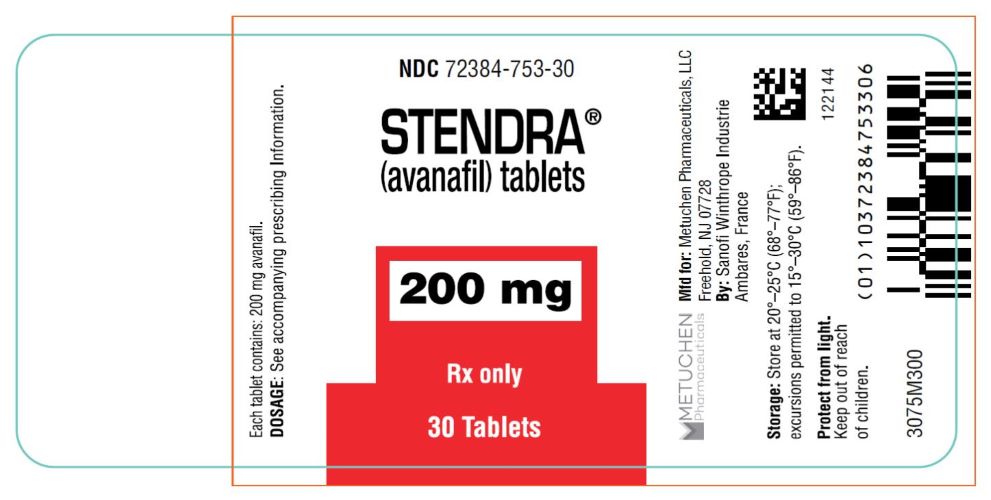 DRUG LABEL: Stendra
NDC: 72384-751 | Form: TABLET
Manufacturer: Metuchen Pharmaceuticals, LLC
Category: prescription | Type: HUMAN PRESCRIPTION DRUG LABEL
Date: 20240718

ACTIVE INGREDIENTS: AVANAFIL 50 mg/1 1
INACTIVE INGREDIENTS: MANNITOL; FUMARIC ACID; HYDROXYPROPYL CELLULOSE, UNSPECIFIED; LOW-SUBSTITUTED HYDROXYPROPYL CELLULOSE (11% HYDROXYPROPYL; 130000 MW); CALCIUM CARBONATE; MAGNESIUM STEARATE; FERRIC OXIDE YELLOW

HIGHLIGHTS OF PRESCRIBING INFORMATION

These highlights do not include all the information needed to use STENDRA safely and effectively. See full prescribing information for STENDRA.
STENDRA® (avanafil) tablets, for oral use
Initial U.S. Approval: 2012

1 INDICATIONS AND USAGE

STENDRA is a phosphodiesterase 5 (PDE5) inhibitor indicated for the treatment of erectile dysfunction (1)

2 DOSAGE AND ADMINISTRATION

- The starting dose is 100 mg taken as early as approximately 15 minutes before sexual activity, on an as needed basis (2.1)
- Take STENDRA no more than once a day (2.1).
- Based on efficacy and/or tolerability, the dose may be increased to 200 mg taken as early as approximately 15 minutes before sexual activity, or decreased to 50 mg taken approximately 30 minutes before sexual activity. Use the lowest dose that provides benefit (2.1).
- STENDRA may be taken with or without food (2.2)
- Do not use STENDRA with strong CYP3A4 inhibitors (2.3)
- If taking a moderate CYP3A4 inhibitor, the dose should be no more than 50 mg in a 24-hour period (2.3).
- In patients on stable alpha-blocker therapy, the recommended starting dose of STENDRA is 50 mg (2.3).

3 DOSAGE FORMS AND STRENGTHS

Tablets: 50 mg, 100 mg, 200 mg (3)

4 CONTRAINDICATIONS

- Administration of STENDRA to patients using any form of organic nitrate is contraindicated (4.1)
- Hypersensitivity to any component of the STENDRA tablet (4.2)
- Administration with guanylate cyclase (GC) stimulators such as riociguat and vericiguat (4.3)

5 WARNINGS AND PRECAUTIONS

- Patients should not use STENDRA if sexual activity is inadvisable due to cardiovascular status or any other reason (5.1)
- Use of STENDRA with alpha-blockers, other antihypertensives, or substantial amounts of alcohol (greater than 3 units) may lead to hypotension (2.3, 5.6, 5.7)
- Patients should seek emergency treatment if an erection lasts greater than 4 hours (5.3)
- Patients should stop STENDRA and seek medical care if a sudden loss of vision occurs in one or both eyes, which could be a sign of Non Arteritic Ischemic Optic Neuropathy (NAION). STENDRA should be used with caution, and only when the anticipated benefits outweigh the risks, in patients with a history of NAION. Patients with a “crowded” optic disc may also be at an increased risk of NAION (5.4, 6.2)
- Patients should stop taking STENDRA and seek prompt medical attention in the event of sudden decrease or loss of hearing (5.5)

6 ADVERSE REACTIONS

Most common adverse reactions (greater than or equal to 2%) include headache, flushing, nasal congestion, nasopharyngitis, and back pain (6.1)

To report SUSPECTED ADVERSE REACTIONS, contact 844.458.4887 or FDA at 1-800-FDA-1088 or www.fda.gov/medwatch.

7 DRUG INTERACTIONS

- STENDRA can potentiate the hypotensive effect of nitrates, alpha-blockers, antihypertensives, and alcohol (7.1)
- CYP3A4 inhibitors (e.g., ketoconazole, ritonavir, erythromycin) increase STENDRA exposure (7.2)

8 USE IN SPECIFIC POPULATIONS

- Do not use in patients with severe renal impairment (8.6)
- Do not use in patients with severe hepatic impairment (8.7)

FULL PRESCRIBING INFORMATION

1 INDICATIONS AND USAGE

STENDRA is a phosphodiesterase 5 (PDE5) inhibitor indicated for the treatment of erectile dysfunction in adult males.

2 DOSAGE AND ADMINISTRATION

2.1 Erectile Dysfunction

The recommended starting dose is 100 mg. STENDRA should be taken orally as needed as early as approximately 15 minutes before sexual activity.

Based on individual efficacy and tolerability, the dose may be increased to 200 mg taken as early as approximately 15 minutes before sexual activity, or decreased to 50 mg taken approximately 30 minutes before sexual activity. The lowest dose that provides benefit should be used.

The maximum recommended dosing frequency is once per day. Sexual stimulation is required for a response to treatment.

2.2 Use with Food

STENDRA may be taken with or without food.

2.3 Concomitant Medications

Nitrates

Concomitant use of nitrates in any form is contraindicated [see Contraindications (4.1)].

Alpha-Blockers

If STENDRA is co-administered with an alpha-blocker, patients should be stable on alpha-blocker therapy prior to initiating treatment with STENDRA, and STENDRA should be initiated at the 50 mg dose [see Warnings and Precautions (5.6), Drug Interactions (7.1) and Clinical Pharmacology (12.2)].

CYP3A4 Inhibitors

- For patients taking concomitant strong CYP3A4 inhibitors (including ketoconazole, ritonavir, atazanavir, clarithromycin, indinavir, itraconazole, nefazodone, nelfinavir, saquinavir and telithromycin), do not use STENDRA [see Warnings and Precautions (5.2) and Drug Interactions (7.2)].
- For patients taking concomitant moderate CYP3A4 inhibitors (including erythromycin, amprenavir, aprepitant, diltiazem, fluconazole, fosamprenavir, and verapamil), the maximum recommended dose of STENDRA is 50 mg, not to exceed once every 24 hours [see Warnings and Precautions (5.2) and Drug Interactions (7.2)].

3 DOSAGE FORMS AND STRENGTHS

STENDRA (avanafil) is supplied as oval, pale yellow tablets containing 50 mg, 100 mg, or 200 mg avanafil debossed with dosage strength.

4 CONTRAINDICATIONS

4.1 Nitrates

Administration of STENDRA with any form of organic nitrates, either regularly and/or intermittently, is contraindicated. Consistent with its known effects on the nitric oxide/cyclic guanosine monophosphate (cGMP) pathway, STENDRA has been shown to potentiate the hypotensive effects of nitrates.

In a patient who has taken STENDRA, where nitrate administration is deemed medically necessary in a life-threatening situation, at least 12 hours should elapse after the last dose of STENDRA before nitrate administration is considered. In such circumstances, nitrates should only be administered under close medical supervision with appropriate hemodynamic monitoring [see Contraindications (4.1), Dosage and Administration (2.3), and Clinical Pharmacology (12.2)].

4.2 Hypersensitivity Reactions

STENDRA is contraindicated in patients with a known hypersensitivity to any component of the tablet. Hypersensitivity reactions have been reported, including pruritis and eyelid swelling.

4.3 Concomitant Guanylate Cyclase (GC) Stimulators

Do not use STENDRA in patients who are using a GC stimulator, such as riociguat or vericiguat. PDE5 inhibitors, including STENDRA may potentiate the hypotensive effects of GC stimulators.

5 WARNINGS AND PRECAUTIONS

Evaluation of erectile dysfunction (ED) should include an appropriate medical assessment to identify potential underlying causes, as well as treatment options.

Before prescribing STENDRA, it is important to note the following:

5.1 Cardiovascular Risks

There is a potential for cardiac risk during sexual activity in patients with pre-existing cardiovascular disease. Therefore, treatments for ED, including STENDRA, should not be used in men for whom sexual activity is inadvisable because of their underlying cardiovascular status.

Patients with left ventricular outflow obstruction (e.g., aortic stenosis, idiopathic hypertrophic subaortic stenosis) and those with severely impaired autonomic control of blood pressure can be particularly sensitive to the actions of vasodilators, including STENDRA.

The following groups of patients were not included in clinical safety and efficacy trials for STENDRA, and therefore until further information is available, STENDRA is not recommended for the following groups:

- Patients who have suffered a myocardial infarction, stroke, life-threatening arrhythmia, or coronary revascularization within the last 6 months;
- Patients with resting hypotension (blood pressure less than 90/50 mmHg) or hypertension (blood pressure greater than 170/100 mmHg);
- Patients with unstable angina, angina with sexual intercourse, or New York Heart Association Class 2 or greater congestive heart failure.

As with other PDE5 inhibitors STENDRA has systemic vasodilatory properties and may augment the blood pressure-lowering effect of other anti-hypertensive medications. STENDRA 200 mg resulted in transient decreases in sitting blood pressure in healthy volunteers of 8.0 mmHg systolic and 3.3 mmHg diastolic [see Clinical Pharmacology (12.2)], with the maximum decrease observed at 1 hour after dosing. While this normally would be expected to be of little consequence in most patients, prior to prescribing STENDRA, physicians should carefully consider whether patients with underlying cardiovascular disease could be affected adversely by such vasodilatory effects, especially in combination with sexual activity.

5.2 Concomitant Use of CYP3A4 Inhibitors

STENDRA metabolism is principally mediated by the CYP450 isoform 3A4 (CYP3A4). Inhibitors of CYP3A4 may reduce STENDRA clearance and increase plasma concentrations of avanafil.

For patients taking concomitant strong CYP3A4 inhibitors (including ketoconazole, ritonavir, atazanavir, clarithromycin, indinavir, itraconazole, nefazodone, nelfinavir, saquinavir and telithromycin), do not use STENDRA [see Drug Interactions (7.2)].

For patients taking concomitant moderate CYP3A4 inhibitors (including erythromycin, amprenavir, aprepitant, diltiazem, fluconazole, fosamprenavir, and verapamil), the maximum recommended dose of STENDRA is 50 mg, not to exceed once every 24 hours [see Drug Interactions (7.2)].

5.3 Prolonged Erection

Prolonged erection greater than 4 hours and priapism (painful erections greater than 6 hours in duration) have been reported with other PDE5 inhibitors. In the event of an erection that persists longer than 4 hours, the patient should seek immediate medical assistance. If not treated immediately, penile tissue damage and permanent loss of potency could result.

STENDRA should be used with caution in patients with anatomical deformation of the penis (such as angulation, cavernosal fibrosis, or Peyronie’s disease), or in patients who have conditions which may predispose them to priapism (such as sickle cell anemia, multiple myeloma, or leukemia).

5.4 Effects on Eye

Physicians should advise patients to stop use of all PDE5 inhibitors, including STENDRA and seek medical attention in the event of a sudden loss of vision in one or both eyes. Such an event may be a sign of non-arteritic anterior ischemic optic neuropathy (NAION), a rare condition and a cause of decreased vision including permanent loss of vision that has been reported rarely postmarketing in temporal association with the use of all PDE5 inhibitors. Based on published literature, the annual incidence of NAION is 2.5-11.8 cases per 100,000 in males aged ≥ 50.

An observational case-crossover study evaluated the risk of NAION when PDE5 inhibitor use, as a class, occurred immediately before NAION onset (within 5 half-lives), compared to PDE5 inhibitor use in a prior time period. The results suggest an approximate 2-fold increase in the risk of NAION, with a risk estimate of 2.15 (95% CI 1.06, 4.34). A similar study reported a consistent result, with a risk estimate of 2.27 (95% CI 0.99, 5.20). Other risk factors for NAION, such as the presence of “crowded” optic disc, may have contributed to the occurrence of NAION in these studies.

Neither the rare postmarketing reports, nor the association of PDE5 inhibitor use and NAION in the observational studies, substantiate a causal relationship between PDE5 inhibitor use and NAION [see Adverse Reactions (6.2)].

Physicians should consider whether their patients with underlying NAION risk factors could be adversely affected by use of PDE5 inhibitors. Individuals who have already experienced NAION are at increased risk of NAION recurrence. Therefore, PDE5 inhibitors, including STENDRA should be used with caution in these patients and only when the anticipated benefits outweigh the risks. Individuals with “crowded” optic disc are also considered at greater risk for NAION compared to the general population; however, evidence is insufficient to support screening of prospective users of PDE5 inhibitors, including STENDRA, for this uncommon condition.

Patients with known hereditary degenerative retinal disorders, including retinitis pigmentosa, were not included in the clinical trials for STENDRA, and therefore, until further information is available, STENDRA is not recommended for use in these patients.

5.5 Sudden Hearing Loss

Use of PDE5 inhibitors has been associated with sudden decrease or loss of hearing, which may be accompanied by tinnitus or dizziness. It is not possible to determine whether these events are related directly to the use of PDE5 inhibitors or to other factors [see Adverse Reactions (6)]. Patients experiencing these symptoms should be advised to stop taking STENDRA and seek prompt medical attention.

5.6 Alpha-Blockers and Other Antihypertensives

Physicians should discuss with patients the potential for STENDRA to augment the blood pressure-lowering effect of alpha-blockers and other antihypertensive medications [see Drug Interactions (7.1) and Clinical Pharmacology (12.2)].

Caution is advised when PDE5 inhibitors are co-administered with alpha-blockers. Phosphodiesterase type 5 inhibitors, including STENDRA, and alpha-adrenergic blocking agents are both vasodilators with blood pressure-lowering effects. When vasodilators are used in combination, an additive effect on blood pressure may be anticipated. In some patients, concomitant use of these two drug classes can lower blood pressure significantly leading to symptomatic hypotension (e.g., dizziness, lightheadedness, fainting).

Consideration should be given to the following:

- Patients should be stable on alpha-blocker therapy prior to initiating treatment with a PDE5 inhibitor. Patients who demonstrate hemodynamic instability on alpha-blocker therapy alone are at increased risk of symptomatic hypotension with concomitant use of PDE5 inhibitors.
- In those patients who are stable on alpha-blocker therapy, PDE5 inhibitors should be initiated at the lowest dose (STENDRA 50 mg).
- In those patients already taking an optimized dose of a PDE5 inhibitor, alpha-blocker therapy should be initiated at the lowest dose. Stepwise increase in alpha-blocker dose may be associated with further lowering of blood pressure when taking a PDE5 inhibitor.

Safety of combined use of PDE5 inhibitors and alpha-blockers may be affected by other variables, including intravascular volume depletion and other anti-hypertensive drugs [see Dosage and Administration (2) and Drug Interactions (7.1)].

5.7 Alcohol

Patients should be made aware that both alcohol and PDE5 inhibitors including STENDRA act as vasodilators. When vasodilators are taken in combination, blood-pressure-lowering effects of each individual compound may be increased. Therefore, physicians should inform patients that substantial consumption of alcohol (e.g., greater than 3 units) in combination with STENDRA may increase the potential for orthostatic signs and symptoms, including increase in heart rate, decrease in standing blood pressure, dizziness, and headache [see Drug Interactions (7.1) and Clinical Pharmacology (12.2)].

5.8 Combination with Other PDE5 Inhibitors or Erectile Dysfunction Therapies

The safety and efficacy of combinations of STENDRA with other treatments for ED has not been studied. Therefore, the use of such combinations is not recommended.

5.9 Effects on Bleeding

The safety of STENDRA is unknown in patients with bleeding disorders and patients with active peptic ulceration. In vitro studies with human platelets indicate that STENDRA potentiates the anti-aggregatory effect of sodium nitroprusside (a nitric oxide [NO] donor).

5.10 Counseling Patients about Sexually Transmitted Diseases

The use of STENDRA offers no protection against sexually transmitted diseases. Counseling patients about the protective measures necessary to guard against sexually transmitted diseases, including Human Immunodeficiency Virus (HIV), should be considered.

6 ADVERSE REACTIONS

6.1 Clinical Trials Experience

Because clinical trials are conducted under widely varying conditions, adverse reaction rates observed in the clinical trials of a drug cannot be directly compared to rates in the clinical trials of another drug and may not reflect the rates observed in practice.

STENDRA was administered to 2215 men during clinical trials. In trials of STENDRA for use as needed, a total of 493 patients were exposed for greater than or equal to 6 months, and 153 patients were treated for greater than or equal to 12 months.

In three randomized, double-blind, placebo-controlled trials lasting up to 3 months in duration, the mean age of patients was 56.4 years (range from 23 to 88 years). 83.9% of patients were White, 13.8% were Black, 1.4% Asian, and < 1% Hispanic. 41.1% were current or previous smokers. 30.6% had diabetes mellitus.

The discontinuation rate due to adverse reactions for patients treated with STENDRA 50 mg, 100 mg, or 200 mg was 1.4%, 2.0%, and 2.0%, respectively, compared to 1.7% for placebo-treated patients.

Table 1 presents the adverse reactions reported when STENDRA was taken as recommended (on an as-needed basis) from these 3 clinical trials.

Table 1: Adverse Reactions Reported by Greater Than or Equal to 2% of Patients Treated with STENDRA From 3 Placebo-Controlled Clinical Trials Lasting 3 Months for STENDRA Use as Needed
Adverse Reaction | Placebo (N = 349) | STENDRA 50 mg (N = 217) | STENDRA 100 mg (N = 349) | STENDRA 200 mg (N = 352)
Headache | 1.7% | 5.1% | 6.9% | 10.5%
Flushing | 0.0% | 3.2% | 4.3% | 4.0%
Nasal congestion | 1.1% | 1.8% | 2.9% | 2.0%
Nasopharyngitis | 2.9% | 0.9% | 2.6% | 3.4%
Back pain | 1.1% | 3.2% | 2.0% | 1.1%

Adverse reactions reported by greater than or equal to 1%, but less than 2% of patients in any STENDRA dose group, and greater than placebo included: upper respiratory infection (URI), bronchitis, influenza, sinusitis, sinus congestion, hypertension, dyspepsia, nausea, constipation, and rash.

In an open-label, long-term extension study of two of these randomized, double-blind, placebo-controlled trials, the total duration of treatment was up to 52 weeks. Among the 712 patients who participated in this open-label extension study, the mean age of the population was 56.4 years (range from 23 to 88 years). The discontinuation rate due to adverse reactions for patients treated with STENDRA (50 mg, 100 mg, or 200 mg) was 2.8%.

In this extension trial, all eligible patients were initially assigned to STENDRA 100 mg. At any point during the trial, patients could request to have their dose of STENDRA increased to 200 mg or decreased to 50 mg based on their individual response to treatment. In total, 536 (approximately 75%) patients increased their dose to 200 mg and 5 (less than 1%) patients reduced their dose to 50 mg.

Table 2 presents the adverse reactions reported when STENDRA was taken as recommended (on an as-needed basis) in this open-label extension trial.

Table 2: Adverse Reactions Reported by Greater Than or Equal to 2% of Patients Treated With STENDRA in an Open-Label Extension Trial
Adverse Reaction | STENDRA (N = 711)
Headache | 5.6%
Flushing | 3.5%
Nasopharyngitis | 3.4%
Nasal congestion | 2.1%

Adverse reactions reported by greater than or equal to 1%, but less than 2% of patients in the open-label extension study included: upper respiratory infection (URI), influenza, sinusitis, bronchitis, dizziness, back pain, arthralgia, hypertension, and diarrhea.

The following events occurred in less than 1% of patients in the three placebo-controlled 3-month clinical trials and/or the open-label, long-term extension study lasting 12 months. A causal relationship to STENDRA is uncertain. Excluded from this list are those events that were minor, those with no plausible relation to drug use and reports too imprecise to be meaningful.

Body as a whole — edema peripheral, fatigue

Cardiovascular — angina, unstable angina, deep vein thrombosis, palpitations

Digestive — gastritis, gastroesophageal reflux disease, hypoglycemia, blood glucose increased, alanine aminotransferase increased, oropharyngeal pain, stomach discomfort, vomiting

Musculoskeletal — muscle spasms, musculoskeletal pain, myalgia, pain in extremity

Nervous — depression, insomnia, somnolence, vertigo

Respiratory — cough, dyspnea exertional, epistaxis, wheezing

Skin and Appendages — pruritus

Urogenital — balanitis, erection increased, hematuria, nephrolithiasis, pollakiuria, urinary tract infection

In an additional, randomized, double-blind, placebo-controlled study lasting up to 3 months in 298 men who had undergone bilateral nerve-sparing radical prostatectomy for prostate cancer, the mean age of patients was 58.4 years (range 40 – 70). Table 3 presents the adverse reactions reported in this additional study.

Table 3: Adverse Reactions Reported by Greater than or Equal to 2% of Patients Treated with STENDRA in a Placebo-Controlled Clinical Trial Lasting 3 Months in Patients Who Underwent Bilateral Nerve-Sparing Radical Prostatectomy (Study 3)
Adverse Reaction | Placebo (N = 100) | STENDRA 100 mg (N = 99) | STENDRA 200 mg (N = 99)
Headache | 1.0% | 8.1% | 12.1%
Flushing | 0.0% | 5.1% | 10.1%
Nasopharyngitis | 0.0% | 3.0% | 5.1%
Upper respiratory infection | 0.0% | 2.0% | 3.0%
Nasal congestion | 1.0% | 3.0% | 1.0%
Back pain | 1.0% | 3.0% | 2.0%
Electrocardiogram abnormal | 0.0% | 1.0% | 3.0%
Dizziness | 0.0% | 1.0% | 2.0%

A randomized, double-blind, placebo-controlled 2 months study was conducted in 435 subjects with a mean age of 58.2 years (range 24 to 86 years) to determine the time to onset of effect of STENDRA, defined as the time to the first occurrence of an erection sufficient for sexual intercourse. Table 4 presents the adverse reactions occurring in ≥ 2% of subjects treated with STENDRA.

Table 4: Adverse Reactions Reported by ≥ 2% of Patients Treated with STENDRA in a Placebo-Controlled Clinical Trial Lasting 2 Months to Determine the Time to Onset of Effect (Study 4)
Adverse Reaction | Placebo (N = 143) | STENDRA 100 mg (N = 146) | STENDRA 200 mg (N = 146)
Headache | 0.7% | 1.4% | 8.9%
Nasal congestion | 0.0% | 0.7% | 4.1%
Gastroenteritis viral | 0.0% | 0.0% | 2.1%

Across all trials with any STENDRA dose, 1 subject reported a change in color vision.

6.2 Postmarketing Experience

The following adverse reactions have been identified during post approval use of STENDRA. Because these reactions are reported voluntarily from a population of uncertain size, it is not always possible to reliably estimate their frequency or establish a causal relationship to drug exposure. These events have been chosen for inclusion either due to their seriousness, reporting frequency, lack of clear alternative causation, or a combination of these factors.

Cardiovascular and cerebrovascular:

Serious cardiovascular and cerebrovascular events, including myocardial infarction, sudden cardiac death, cerebrovascular accident, and subarachnoid hemorrhage, have been reported post-marketing in temporal association with the use of STENDRA. All of these patients had preexisting cardiovascular risk factors. The occurrence of sexual activity was not stated in the majority of reports, although events were reported to occur both with and without sexual activity. It is not possible to determine whether these events are related directly to STENDRA, to sexual activity, to the patient’s underlying cardiovascular disease, to a combination of these factors, or to other factors [see Warnings and Precautions (5.1) and Patient Counseling Information (17.2)].

Nervous: transient global amnesia

Special senses:

Ophthalmologic: vitreous detachment, visual impairment

Non-arteritic anterior ischemic optic neuropathy (NAION), a cause of decreased vision including permanent loss of vision, has been reported rarely post-marketing in temporal association with the use of phosphodiesterase type 5 (PDE5) inhibitors, such as STENDRA. Most, but not all, of these patients had underlying anatomic or vascular risk factors for developing NAION, including but not necessarily limited to: low cup to disc ratio (“crowded disc”), age over 50, diabetes, hypertension, coronary artery disease, hyperlipidemia and smoking [see Warnings and Precautions (5.4)].

Otologic: Cases of sudden decrease or loss of hearing have been reported postmarketing in temporal association with the use of PDE5 inhibitors, such as STENDRA. In some of the cases, medical conditions and other factors were reported that may have also played a role in the otologic adverse events. In many cases, medical follow-up information was limited. It is not possible to determine whether these reported events are related directly to the use of PDE5 inhibitors such as STENDRA, to the patient’s underlying risk factors for hearing loss, a combination of these factors, or to other factors [see Warnings and Precautions (5.5) and Patient Counseling Information (17.6)].

7 DRUG INTERACTIONS

7.1 Potential for Pharmacodynamic Interactions with STENDRA

Nitrates

Administration of STENDRA to patients who are using any form of organic nitrate, is contraindicated. In a clinical pharmacology trial, STENDRA was shown to potentiate the hypotensive effect of nitrates. In a patient who has taken STENDRA, where nitrate administration is deemed medically necessary in a life-threatening situation, at least 12 hours should elapse after the last dose of STENDRA before nitrate administration is considered. In such circumstances, nitrates should only be administered under close medical supervision with appropriate hemodynamic monitoring [see Contraindications (4.1), Dosage and Administration (2.3), and Clinical Pharmacology (12.2)].

Alpha-Blockers

Caution is advised when PDE5 inhibitors are co-administered with alpha-blockers. PDE5 inhibitors, including STENDRA, and alpha-adrenergic blocking agents are both vasodilators with blood pressure-lowering effects. When vasodilators are used in combination, an additive effect on blood pressure may be anticipated. In some patients, concomitant use of these two drug classes can lower blood pressure significantly leading to symptomatic hypotension (e.g., dizziness, lightheadedness, fainting) [see Warnings and Precautions (5.6), Dosage and Administration (2.3), and Clinical Pharmacology (12.2)].

Antihypertensives

PDE5 inhibitors, including STENDRA, are mild systemic vasodilators. A clinical pharmacology trial was conducted to assess the effect of STENDRA on the potentiation of the blood pressure-lowering effects of selected antihypertensive medications (amlodipine and enalapril). Additional reductions in blood pressure of 3 to 5 mmHg occurred following co-administration of a single 200 mg dose of STENDRA with these agents compared with placebo [see Warnings and Precautions (5.6) and Clinical Pharmacology (12.2)].

Alcohol

Both alcohol and PDE5 inhibitors, including STENDRA, act as vasodilators. When vasodilators are taken in combination, blood pressure-lowering effects of each individual compound may be increased. Substantial consumption of alcohol (e.g., greater than 3 units) in combination with STENDRA can increase the potential for orthostatic signs and symptoms, including increase in heart rate, decrease in standing blood pressure, dizziness, and headache [see Clinical Pharmacology (12.2)].

7.2 Potential for Other Drugs to Affect STENDRA

STENDRA is a substrate of and predominantly metabolized by CYP3A4. Studies have shown that drugs that inhibit CYP3A4 can increase avanafil exposure.

Strong CYP3A4 Inhibitors

Ketoconazole (400 mg daily), a selective and strong inhibitor of CYP3A4, increased STENDRA 50 mg single-dose systemic exposure (AUC) and maximum concentration (Cmax) equal to 13-fold and 3-fold, respectively, and prolonged the half-life of avanafil to approximately 9 hours. Other potent inhibitors of CYP3A4 (e.g., itraconazole, clarithromycin, nefazadone, ritonavir, saquinavir, nelfinavir, indinavir, atanazavir and telithromycin) would be expected to have similar effects. Do not use STENDRA in patients taking strong CYP3A4 inhibitors [see Warnings and Precautions (5.2) and Dosage and Administration (2.3)].

HIV Protease inhibitor — Ritonavir (600 mg twice daily), a strong CYP3A4 inhibitor, which also inhibits CYP2C9, increased STENDRA 50 mg single-dose Cmax and AUC equal to approximately 2-fold and 13-fold, and prolonged the half-life of avanafil to approximately 9 hours in healthy volunteers. Do not use STENDRA in patients taking ritonavir.

Moderate CYP 3A4 Inhibitors

Erythromycin (500 mg twice daily) increased STENDRA 200 mg single-dose Cmax and AUC equal to approximately 2-fold and 3-fold, respectively, and prolonged the half-life of avanafil to approximately 8 hours in healthy volunteers. Moderate CYP3A4 inhibitors (e.g., erythromycin, amprenavir, aprepitant, diltiazem, fluconazole, fosamprenavir, and verapamil) would be expected to have similar effects. Consequently, the maximum recommended dose of STENDRA is 50 mg, not to exceed once every 24 hours for patients taking concomitant moderate CYP3A4 inhibitors [see Warnings and Precautions (5.2) and Drug Interactions (7.2)].

Although specific interactions have not been studied, other CYP3A4 inhibitors, including grapefruit juice are likely to increase avanafil exposure.

Weak CYP3A4 Inhibitors

No in vivo drug-drug interaction studies with weak CYP3A4 inhibitors were conducted.

CYP3A4 Substrate

When administered with STENDRA 200 mg, amlodipine (5 mg daily) increased the Cmax and AUC of avanafil by approximately 22% and 70%, respectively. The half-life of STENDRA was prolonged to approximately 10 hrs. The Cmax and AUC of amlodipine decreased by approximately 9% and 4%, respectively [see Dosage and Administration (2.3)].

Cytochrome P450 Inducers

The potential effect of CYP inducers on the pharmacokinetics of avanafil was not evaluated. The concomitant use of STENDRA and CYP inducers is not recommended.

8 USE IN SPECIFIC POPULATIONS

8.1 Pregnancy

Risk Summary

STENDRA is not indicated for use in females.

There are no data with the use of STENDRA in pregnant women to inform any drug-associated risks for adverse developmental outcomes. In animal reproduction studies conducted in pregnant rats and rabbits, no adverse developmental outcomes were observed with oral administration of avanafil during organogenesis at exposures for total avanafil at approximately 8 and 6 times, respectively, the Maximum Recommended Human Dose (MRHD) of 200 mg based on AUC (see Data).

Data

Animal Data

In pregnant rats administered orally at 100, 300, or 1000 mg/kg/day from gestation days 6 to 17, no evidence of teratogenicity, embryotoxicity, or fetotoxicity was observed at up to 300 mg/kg/day. This dose is equivalent to exposures of approximately 8 times the exposure at the Maximum Recommended Human Dose (MRHD) of 200 mg based on AUCs for total avanafil. At the maternally toxic dose (1000 mg/kg/day), decreased fetal body weight occurred with no signs of teratogenicity. In pregnant rabbits administered orally at 30, 60, 120, or 240 mg/kg/day from gestation days 6 to 18, no teratogenicity was observed at exposures up to approximately 6 times the human exposure at the MRHD based on AUCs for total avanafil.

In a pre- and post-natal development study in rats given orally at 100, 300, or 600 mg/kg/day on gestation days 6 through lactation day 20, offspring growth and maturation were reduced when maternal rats were given avanafil doses greater than or equal to 300 mg/kg/day, resulting in exposures greater than or equal to 17 times the human exposure to total avanafil at the MRHD. There was no effect on reproductive performance of the maternal rats or offspring, or on the behavior of the offspring at up to the highest dose tested. The no observed adverse effect level (NOAEL) for developmental toxicity (100 mg/kg/day) was observed at exposures to total avanafil approximately 2-fold greater than the systemic exposure in humans at the MRHD.

8.2 Lactation

Risk Summary

STENDRA is not indicated for use in females.

There is no information on the presence of avanafil and/or its metabolites in human or animal milk, the effects on the breastfed child, or the effects on milk production.

8.3 Females and Males of Reproductive Potential

Infertility

There have been no studies evaluating the effect of STENDRA on fertility in men [see Clinical Pharmacology (12.2)]

Based on studies in animals, decreased fertility, abnormal sperm motility and morphology, and altered estrous cycles were observed in rats. The abnormal sperm findings were reversible at the end of a 9-week drug-free period [see Nonclinical Toxicology (13.1)].

8.4 Pediatric Use

STENDRA is not indicated for use in pediatric patients. Safety and efficacy in patients below the age of 18 years has not been established.

8.5 Geriatric Use

Of the total number of subjects in clinical studies of avanafil, approximately 23% were 65 and over. No overall differences in efficacy and safety were observed between subjects over 65 years of age compared to younger subjects; therefore, no dose adjustment is warranted based on age alone. However, a greater sensitivity to medication in some older individuals should be considered [see Clinical Pharmacology (12.3)].

8.6 Renal Impairment

In a clinical pharmacology trial using single 200 mg doses of STENDRA, avanafil exposure (AUC or Cmax) in normal subjects was comparable to patients with mild (creatinine clearance greater than or equal to 60 to less than 90 mL/min) or moderate (creatinine clearance greater than or equal to 30 to less than 60 mL/min) renal impairment. No dose adjustment is necessary for patients with mild to moderate renal impairment (creatinine clearance greater than or equal to 30 to less than 90 mL/min). The pharmacokinetics of avanafil in patients with severe renal disease or on renal dialysis has not been studied; do not use STENDRA in such patients [see Clinical Pharmacology (12.3)].

8.7 Hepatic Impairment

In a clinical pharmacology trial, avanafil AUC and Cmax in patients with mild hepatic impairment (Child-Pugh Class A) was comparable to that in healthy subjects when a dose of 200 mg was administered. Avanafil Cmax was approximately 51% lower and AUC was 11% higher in patients with moderate hepatic impairment (Child Pugh Class B) compared to subjects with normal hepatic function. No dose adjustment is necessary for patients with mild to moderate hepatic impairment (Child Pugh Class A or B). The pharmacokinetics of avanafil in patients with severe hepatic disease has not been studied; do not use STENDRA in such patients [see Clinical Pharmacology (12.3)].

10 OVERDOSAGE

Single doses up to 800 mg have been given to healthy subjects, and multiple doses up to 300 mg have been given to patients. In cases of overdose, standard supportive measures should be adopted as required. Renal dialysis is not expected to accelerate clearance because avanafil is highly bound to plasma proteins and is not significantly eliminated in the urine.

11 DESCRIPTION

STENDRA (avanafil) is a selective inhibitor of cGMP-specific PDE5.

Avanafil is designated chemically as (S)-4-[(3-Chloro-4-methoxybenzyl)amino]-2-[2-(hydroxymethyl)-1-pyrrolidinyl]-N-(2-pyrimidinylmethyl)-5-pyrimidinecarboxamide and has the following structural formula:

Avanafil occurs as white crystalline powder, molecular formula C23 H26 ClN7 O3 and molecular weight of 483.95 and is slightly soluble in ethanol, practically insoluble in water, soluble in 0.1 mol/L hydrochloric acid. STENDRA, for oral administration, is supplied as oval, pale yellow tablets containing 50 mg, 100 mg, or 200 mg avanafil debossed with dosage strengths. In addition to the active ingredient, avanafil, each tablet contains the following inactive ingredients: mannitol, fumaric acid, hydroxypropylcellulose, low substituted hydroxypropylcellulose, calcium carbonate, magnesium stearate, and ferric oxide yellow.

12 CLINICAL PHARMACOLOGY

12.1 Mechanism of Action

The physiologic mechanism of erection of the penis involves release of nitric oxide (NO) in the corpus cavernosum during sexual stimulation. NO then activates the enzyme guanylate cyclase, which results in increased levels of cGMP, producing smooth muscle relaxation in the corpus cavernosum and allowing inflow of blood. Avanafil has no direct relaxant effect on isolated human corpus cavernosum, but enhances the effect of NO by inhibiting PDE5, which is responsible for degradation of cGMP in the corpus cavernosum. Because sexual stimulation is required to initiate the local release of nitric oxide, the inhibition of PDE5 has no effect in the absence of sexual stimulation.

Studies in vitro have shown that avanafil is selective for PDE5. Its effect is more potent on PDE5 than on other known phosphodiesterases (greater than 100-fold for PDE6; greater than 1,000-fold for PDE4, PDE8 and PDE10; greater than 5,000-fold for PDE2 and PDE7; greater than 10,000-fold for PDE1, PDE3, PDE9, and PDE11). Avanafil is greater than 100-fold more potent for PDE5 than PDE6, which is found in the retina and is responsible for phototransduction. In addition to human corpus cavernosum smooth muscle, PDE5 is also found in other tissues including platelets, vascular and visceral smooth muscle, and skeletal muscle, brain, heart, liver, kidney, lung, pancreas, prostate, bladder, testis, and seminal vesicle. The inhibition of PDE5 in these tissues by avanafil may be the basis for the enhanced platelet anti-aggregatory activity of NO observed in vitro and peripheral vasodilatation in vivo.

12.2 Pharmacodynamics

Effects of STENDRA on Erectile Response

In a single-blind, placebo-controlled, single-dose trial of 82 patients with either organic and/or psychogenic ED, visual sexual stimulation resulted in improved erections after STENDRA administration compared to placebo, as assessed by an objective measurement of hardness and duration of erections (RigiScan®). Efficacy was assessed by RigiScan at discrete time intervals ranging from 20 – 40 minutes after dosing to 100 – 120 minutes after dosing.

Effects of STENDRA on Blood Pressure

Single oral doses of STENDRA (200 mg) administered to healthy male volunteers resulted in mean changes from baseline in systolic/diastolic blood pressure of -5.3/-3.7 mmHg at 1 hour after dosing, compared to mean changes from baseline in the placebo group of 2.7/-0.4 mmHg. The reductions in systolic/diastolic blood pressure at 1 hour after dosing of STENDRA 200 mg compared to placebo were 8.0/3.3 mmHg.

Figure 1: Median Change from Baseline in Sitting Systolic Blood Pressure, Healthy Volunteers Day 4

Effects on Cardiac Electrophysiology

The effect of single 100 or 800 mg doses of STENDRA on the QT interval were evaluated in a randomized, double-blind, placebo, and active (moxifloxacin) –controlled crossover study in 52 healthy male subjects aged 18 to 45 years. There were no significant effects of the 100 mg dose. The mean QTc (Fridericia QT correction) for avanafil 800 mg, relative to placebo was 9.4 milliseconds (two-sided 90% CI=7.2, 11.6). An 800 mg dose of STENDRA (4 times the highest recommended dose) was chosen because this dose yields exposures greater than those observed upon co-administration of avanafil with strong CYP3A4 inhibitors. A double-blind, randomized, placebo- and active-controlled (moxifloxacin), thorough QT/QTc trial of STENDRA (100 and 800 mg) in healthy male subjects demonstrated that STENDRA did not cause any significant changes in QTc interval or ventricular repolarization.

Effects of STENDRA on Blood Pressure When Administered with Nitrates

In a clinical pharmacology trial, a single dose of STENDRA 200 mg was shown to potentiate the hypotensive effect of nitrates. The use of STENDRA in patients taking any form of nitrates is contraindicated [see Contraindications (4.1)].

A trial was conducted to assess the degree of interaction between nitroglycerin and STENDRA, should nitroglycerin be required in an emergency situation after STENDRA was taken. This was a single-center, double-blind, randomized, 3-way crossover trial of healthy males from 30 to 60 years of age. Subjects were divided among 5 trial groups with the trial group being determined by the time interval between treatment with trial drug and glyceryl trinitrate administration. Subjects were assigned to trial groups sequentially and hemodynamic results from the previous group were reviewed for serious adverse events (SAEs) before the next group received treatment. Each subject was dosed with all 3 study drugs (STENDRA 200 mg, sildenafil citrate 100 mg, and placebo) in random order. Subjects were administered a single dose of 0.4 mg sublingual nitroglycerin (NTG) at pre-specified time points, following their dose of trial drug (0.5, 1, 4, 8 or 12 hours). Overall, 14 (15%) subjects treated with placebo and 28 (28%) subjects treated with avanafil, had clinically significant decreases in standing SBP, defined as greater than or equal to 30 mmHg decrease in SBP, after glyceryl trinitrate administration. Mean maximum decreases are shown in Table 5.

Table 5: Mean Maximum Decreases from Baseline in Sitting and Standing Systolic Blood Pressure/Diastolic Blood Pressure (mmHg) following Placebo or 200 mg STENDRA with 0.4 mg sublingual nitroglycerin
Placebo with nitroglycerin Sitting Standing | 13.4/11.8 21.1/16.5
STENDRA with nitroglycerin Sitting Standing | 21.6/18.2 28.0/23.5

Like other PDE5 inhibitors, STENDRA administration with nitrates is contraindicated. In a patient who has taken STENDRA, where nitrate administration is deemed medically necessary in a life threatening situation, at least 12 hours should elapse after the last dose of STENDRA before nitrate administration is considered. In such circumstances, nitrates should still only be administered under close medical supervision with appropriate hemodynamic monitoring [see Contraindications (4.1)].

Effects of STENDRA on Blood Pressure When Administered with Alpha-Blockers

A single-center, randomized, double-blinded, placebo-controlled, two-period crossover trial was conducted to investigate the potential interaction of STENDRA with alpha-blocker agents in healthy male subjects which consisted of two cohorts:

Cohort A (N=24): Subjects received oral doses of doxazosin once daily in the morning at 1 mg for 1 day (Day 1), 2 mg for 2 days (Days 2 – 3), 4 mg for 4 days (Days 4 – 7), and 8 mg for 11 days (Days 8 – 18). On Days 15 and 18, the subjects also received a single oral dose of either 200 mg STENDRA or placebo, according to the treatment randomization code. The STENDRA or placebo doses were administered 1.3 hours after the doxazosin administration on Days 15 and 18. The co-administration was designed so that doxazosin (Tmax ~2 hours) and STENDRA (Tmax ~0.7 hours) would reach their peak plasma concentrations at the same time.

Cohort B (N=24): Subjects received 0.4 mg daily oral doses of tamsulosin in the morning for 11 consecutive days (Days 1 – 11). On Days 8 and 11, the subjects also received a single oral dose of either 200 mg STENDRA or placebo, according to the treatment randomization code. The STENDRA or placebo doses were administered 3.3 hours after the tamsulosin administration on Days 8 and 11. The co-administration was designed so that tamsulosin (Tmax ~4 hours) and STENDRA (Tmax ~0.7 hours) would reach their peak plasma concentrations at the same time.

Supine and sitting BP and pulse rate measurements were recorded before and after STENDRA or placebo dosing.

A total of seven subjects in Cohort A (doxazosin) experienced potentially clinically important absolute values or changes from baseline in standing SBP or DBP. Three subjects experienced standing SBP values less than 85 mmHg. One subject experienced a decrease from baseline in standing SBP greater than 30 mmHg following STENDRA. Two subjects experienced standing DBP values less than 45 mmHg following STENDRA. Four subjects experienced decreases from baseline in standing DBP greater than 20 mmHg following STENDRA. One subject experienced such decreases following placebo. There were no severe adverse events related to hypotension reported during the trial. There were no cases of syncope.

A total of five subjects in Cohort B (tamsulosin) experienced potentially clinically important absolute values or changes from baseline in standing SBP or DBP. Two subjects experienced standing SBP values less than 85 mmHg following STENDRA. One subject experienced a decrease from baseline in standing SBP greater than 30 mmHg following STENDRA. Two subjects experienced standing DBP values less than 45 mmHg following STENDRA. Four subjects experienced decreases from baseline in standing DBP greater than 20 mmHg following STENDRA; one subject experienced such decreases following placebo. There were no severe adverse events related to hypotension reported during the trial. There were no cases of syncope.

Table 6 presents the placebo-subtracted mean maximum decreases from baseline (95% CI) in systolic blood pressure results for the 24 subjects who received STENDRA 200 mg and matching placebo.

Table 6: Placebo-Subtracted Mean (95% CI) Maximum Decreases from Baseline in Standing and Supine Systolic Blood Pressure (mmHg) with 200 mg STENDRA
Doxazosin Supine Standing | -6.0 (-9.1, -2.9) -2.5 (-6.5, 1.5)
Tamsulosin Supine Standing | -3.1 (-6.4, 0.1) -3.6 (-8.1, 0.9)

Blood pressure effects (standing SBP) in normotensive men on stable dose doxazosin (8 mg) following administration of STENDRA 200 mg or placebo, are shown in Figure 2. Blood pressure effects (standing SBP) in normotensive men on stable dose tamsulosin (0.4 mg) following administration of STENDRA 200 mg or placebo are shown in Figure 3.

Figure 2: Mean (SD) Change From Baseline in Standing Systolic Blood Pressure Over Time Following Administration of a Single Dose 200 mg Dose of STENDRA with Doxazosin

Figure 3: Mean (SD) Change From Baseline in Standing Systolic Blood Pressure Over Time Following Administration of a Single Dose 200 mg Dose of STENDRA with Tamsulosin

Effects of STENDRA on Blood Pressure When Administered with Enalapril

A trial was conducted to assess the interaction of enalapril (20 mg daily) and STENDRA 200 mg. Single doses of 200 mg STENDRA co-administered with enalapril caused a mean maximum decrease in supine systolic/diastolic blood pressure of 1.8/3.5 mmHg (compared to placebo), accompanied by a mean maximum increase in pulse rate of 1.0 bpm.

Effects of STENDRA on Blood Pressure When Administered with Amlodipine

A trial was conducted to assess the interaction of amlodipine (5 mg daily) and STENDRA 200 mg. Single doses of 200 mg STENDRA co-administered with amlodipine caused a mean maximum decrease in supine systolic blood pressure of 1.2 mmHg (compared to placebo), accompanied by a mean maximum increase in pulse rate of 1.0 bpm; the mean maximum decrease in diastolic blood pressure was less than that observed in the placebo group. There was no effect of STENDRA on amlodipine plasma concentrations. Concomitant amlodipine was associated with 22% and 70% increases in avanafil Cmax and AUC, respectively.

Effects of STENDRA on Blood Pressure When Administered with Alcohol

Alcohol and PDE5 inhibitors, including STENDRA, are mild systemic vasodilators. The interaction of STENDRA with alcohol was evaluated in a clinical pharmacology trial. Alcohol was administered at a dose of 0.5 g/kg, which is equivalent to approximately 3 ounces of 80-proof vodka in a 70-kg male, and STENDRA was administered at a dose of 200 mg. All patients consumed the entire alcohol dose within 15 minutes of starting. Blood alcohol levels of 0.057% were confirmed. There were no reports of orthostatic hypotension or dizziness. Additional maximum supine systolic/diastolic blood pressure decreases of 3.5/4.5 mmHg and additional maximum pulse rate increase of 9.3 bpm were observed when avanafil was taken with alcohol compared to alcohol alone. Avanafil did not affect alcohol plasma concentrations.

Effects of STENDRA on Spermatogenesis

The effect of STENDRA on spermatogenesis was assessed in 181 healthy male volunteers who received STENDRA 100 mg or placebo daily for 26 weeks. The results of this randomized, double-blind, placebo-controlled study in 137 subjects who completed the study through Week 26 and provided 2 semen samples at baseline and at Week 26 showed no adverse effects of STENDRA on sperm concentration, total sperm count, sperm motility, sperm normal morphology, and semen volume.

Effects of STENDRA on Vision

Single oral doses of Type 5 phosphodiesterase inhibitors have demonstrated transient dose-related impairment of color discrimination (blue/green), using the Farnsworth-Munsell 100-hue test, with peak effects near the time of peak plasma levels. This finding is consistent with the inhibition of PDE6, which is involved in phototransduction in the retina.

12.3 Pharmacokinetics

Mean STENDRA plasma concentrations measured after the administration of a single oral dose of 50 or 200 mg to healthy male volunteers are depicted in Figure 4. The pharmacokinetics of STENDRA are dose proportional from 12.5 to 600 mg.

Figure 4: Plasma Avanafil Concentrations (mean ± SD) Following a Single 50 mg or 200 mg STENDRA Dose

Absorption and Distribution

STENDRA is rapidly absorbed after oral administration, with a median Tmax of 30 to 45 minutes in the fasted state. When STENDRA (200 mg) is taken with a high fat meal, the rate of absorption is reduced, with a mean delay in Tmax of 1.12 to 1.25 hours and a mean reduction in Cmax of 39% (200 mg). There was an approximate 3.8% decrease in AUC. The small changes in avanafil Cmax and AUC are considered of minimal clinical significance; therefore, STENDRA may be administered with or without food. The mean accumulation ratio is approximately 1.2. Avanafil is approximately 99% bound to plasma proteins. Protein binding is independent of total drug concentrations, age, renal and hepatic function.

Based upon measurements of avanafil in semen of healthy volunteers 45-90 minutes after dosing, less than 0.0002% of the administered dose appeared in the semen of patients.

Metabolism and Excretion

Avanafil is cleared predominantly by hepatic metabolism, mainly by the CYP3A4 enzyme and to a minor extent by CYP2C isoform. The plasma concentrations of the major circulating metabolites, M4 and M16, are approximately 23% and 29% that of the parent compound, respectively. The M4 metabolite has an in vitro inhibitory potency for PDE5 18% of that of avanafil and M4 accounts for approximately 4% of the pharmacologic activity of avanafil. The M16 metabolite was inactive against PDE5.

Avanafil was extensively metabolized in humans. After oral administration, avanafil is excreted as metabolites predominantly in the feces (approximately 62% of administered oral dose) and to a lesser extent in the urine (approximately 21% of the administered oral dose). STENDRA has a terminal elimination half-life of approximately 5 hours.

Geriatric

The pharmacokinetics of a single 200 mg STENDRA administered to fourteen healthy elderly male volunteers (65-80 years) and eighteen healthy younger male volunteers (18-43 years of age) were compared. AUC0-inf increased by 6.8% and Cmax decreased by 2.1% in the elderly group, compared to the younger group. However, greater sensitivity to medications in some older individuals should be considered [see Use in Specific Populations (8.5)].

Renal Impairment

The pharmacokinetics of a single 200 mg STENDRA administered to nine patients with mild (creatinine clearance greater than or equal to 60 and less than 90 mL/min) and to ten patients with moderate (creatinine clearance greater than or equal to 30 to less than 60 mL/min) renal impairment were evaluated. AUC0-inf decreased by 2.9% and Cmax increased by 2.8% in patients with mild renal impairment, compared to healthy volunteers with normal renal function. AUC0-inf increased by 9.1% and Cmax decreased by 2.8% in patients with moderate renal impairment, compared to healthy volunteers with normal renal function. There is no data available for subjects with severe renal insufficiency or end-stage renal disease on hemodialysis [see Use in Specific Populations (8.6)].

Hepatic Impairment

The pharmacokinetics of a single 200 mg STENDRA administered to eight patients with mild hepatic impairment (Child-Pugh A) and eight patients with moderate hepatic impairment (Child-Pugh B) were evaluated. AUC0-inf increased by 3.8% and Cmax decreased by 2.7% in patients with mild hepatic impairment, compared to healthy volunteers with normal hepatic function. AUC0-inf increased by 11.2% and Cmax decreased by 51% in patients with moderate hepatic impairment, compared to healthy volunteers with normal hepatic function. There is no data available for subjects with severe hepatic impairment (Child-Pugh Class C) [see Use in Specific Populations (8.7)].

Drug Interaction Studies

Clinical Studies

Effect of CYP3A4 Inhibitors on Avanafil: Strong and moderate CYP3A4 inhibitors increase plasma concentrations of STENDRA. The effect of strong CYP3A4 inhibitors, ketoconazole and ritonavir, and moderate CYP3A4 inhibitor, erythromycin, on avanafil pharmacokinetics was studied in an open-label, randomized, one-sequence crossover, three-way parallel study.

Strong CYP3A4 Inhibitors

Fifteen healthy male volunteers received 400 mg ketoconazole (2 tablets containing 200 mg ketoconazole) once daily for 5 days (Days 2-6) and a single 50 mg avanafil on Days 1 and 6. Twenty-four hour pharmacokinetics of avanafil on Days 1 and 6 were compared. Co-administration with the strong CYP3A4 inhibitor ketoconazole resulted in an approximate 13-fold increase in AUC0-inf and 3.1-fold increase in Cmax. Fourteen healthy male volunteers received 300 mg ritonavir (3 tablets containing 100 mg ritonavir) twice daily for 1 day (Day 2), 400 mg twice daily for 1 day (Day 3), 600 mg twice daily for 5 days (Days 4-8), and a single 50 mg avanafil on Days 1 and 8. Twenty-four hour pharmacokinetics of avanafil on Days 1 and 8 were compared. Co-administration with the strong CYP3A4 inhibitor ritonavir resulted in an approximate 13-fold increase in AUC0-inf and 2.4-fold increase in Cmax of avanafil.

Moderate CYP3A4 Inhibitors

Fifteen healthy male volunteers received 500 mg erythromycin (2 tablets containing 250 mg erythromycin) every 12 hrs for 5 days (Days 2-6) and a single 200 mg avanafil (2 tablets containing 100 mg avanafil) on Days 1 and 6. Twenty-four hour pharmacokinetics of avanafil on Days 1 and 6 were compared. Co-administration with the moderate CYP3A4 inhibitor erythromycin resulted in an approximate 3.6-fold increase in AUC0-inf and 2.0-fold increase in Cmax of avanafil.

Effect of Avanafil on Other Drugs:

Warfarin

The effect of avanafil on warfarin pharmacokinetics and pharmacodynamics was evaluated in a double-blind, randomized, placebo-controlled, two-way crossover study. Twenty-four healthy male volunteers were randomized to receive either 200 mg avanafil or matching placebo for 9 days. On Day 3 of each period, volunteers received a single 25 mg warfarin. Pharmacokinetics of R- and S-warfarin, PT, and INR prior to warfarin dosing and up to 168 hrs after warfarin administration were compared. Platelet aggregation prior to warfarin dosing and up to 24 hrs after warfarin administration were compared. PT, INR, and platelet aggregation did not change with avanafil administration: 23.1 sec, 2.2, and 75.5%, respectively. Co-administration with avanafil resulted in an approximate 1.6% increase in AUC0-inf and 5.2% decrease in Cmax of S-warfarin.

Omeprazole, Rosiglitazone, and Desipramine

The effect of avanafil on the pharmacokinetics of omeprazole (a CYP2C19 substrate), rosiglitazone (a CYP2C8 substrate), and desipramine (a CYP2D6 substrate) was evaluated in an open-label, three cohort, crossover study. Nineteen healthy male volunteers received a single 40 mg omeprazole delayed-release capsule once daily for 8 days (Days 1-8), and a single 200 mg avanafil on Day 8. Twelve hour pharmacokinetics of omeprazole on Days 7 and 8 were compared. Co-administration with avanafil resulted in an approximate 5.9% increase in AUC0-inf and 8.6% increase in Cmax of omeprazole. Twenty healthy male volunteers received a single 8 mg rosiglitazone tablet then a single 200 mg avanafil. Twenty-four hour pharmacokinetics of rosiglitazone with and without avanafil were compared. Co-administration with avanafil resulted in an approximate 2.0% increase in AUC0-inf and 14% decrease in Cmax of rosiglitazone. Twenty healthy male volunteers received a single 50 mg desipramine tablet then a single 200 mg avanafil tablet 2 hours after desipramine. Ninety-six hour pharmacokinetics of desipramine with and without avanafil were compared. Co-administration with avanafil resulted in an approximate 5.7% increase in AUC0-inf and 5.2% increase in Cmax of desipramine.

In vitro studies

Avanafil had no effect on CYP1A1/2, 2A6, 2B6 and 2E1 (IC50 greater than 100 micromolar) and weak inhibitory effects toward other isoforms (CYP2C8, 2C9, 2C19, 2D6, 3A4). Major circulating metabolites of avanafil (M4 and M16) had no effect on CYPs 1A, 2A6, 2B6, 2C8, 2C9, 2C19, 2D6, 2E1 and 3A4. Avanafil and its metabolites (M4 and M16) are unlikely to cause clinically significant inhibition of CYPs 1A, 2A6, 2B6, 2C8, 2C9, 2C19, 2D6, 2E1 or 3A4.

13 NONCLINICAL TOXICOLOGY

13.1 Carcinogenesis, Mutagenesis and Impairment of Fertility

Carcinogenesis

Avanafil was not carcinogenic to CD-1 mice when administered daily at doses of 100, 200, or 600 mg/kg/day orally by gavage for at least 98 weeks (approximately 11 times the MRHD on an AUC basis) or to Sprague Dawley rats when administered daily at doses of 100, 300, or 1000 mg/kg/day orally by gavage for at least 100 weeks (approximately 8 times for males and 34 times for females above the MRHD on an AUC basis).

Mutagenesis

Avanafil was not genotoxic in a series of tests. Avanafil was not mutagenic in Ames assays. Avanafil was not clastogenic in chromosome aberration assays using Chinese hamster ovary and lung cells, or in vivo in the mouse micronucleus assay. Avanafil did not affect DNA repair when tested in the rat unscheduled DNA synthesis assay.

Impairment of Fertility

In a rat fertility and early embryonic development study administered 100, 300, or 1000 mg/kg/day for 28 days prior to pairing and continued until euthanasia for males, and 14 days prior to pairing to gestation day 7 for females, a decrease in fertility, no or reduced sperm motility, altered estrous cycles, and an increased percentage of abnormal sperm (broken sperm with detached heads) occurred at exposures in males approximately 11 times the human exposure at a dose of 200 mg. The altered sperm effects were reversible at the end of a 9-week drug-free period. Systemic exposure at the NOAEL (300 mg/kg/day) was comparable to the human AUC at the MRHD of 200 mg.

13.2 Animal Toxicology and/or Pharmacology

Repeated oral administration of avanafil in multiple species resulted in signs of centrally-mediated toxicity including ataxia, tremor, convulsion, hypoactivity, recumbency, and/or prostration at doses resulting in exposures approximately 5-8 times the MRHD based on Cmax and 8-30 times the MRHD based on AUC.

14 CLINICAL STUDIES

STENDRA was evaluated in four randomized, double-blind, placebo-controlled, parallel trials of 2 to 3 months in duration. STENDRA was taken as needed at doses of 50 mg, 100 mg, and 200 mg (Study 1) and 100 mg and 200 mg (Study 2, Study 3 and Study 4). Patients were instructed to take 1 dose of study drug approximately 30 minutes (Study 1 and Study 2) or approximately 15 minutes (Study 4) prior to initiation of sexual activity. Food and alcohol intake was not restricted.

In addition, a subset of patients from 2 of these trials were enrolled into an open-label extension trial. In the open-label extension trial, all eligible patients were initially assigned to avanafil 100 mg. At any point during the trial, patients could request to have their dose of avanafil increased to 200 mg or decreased to 50 mg based on their individual response to treatment.

The 3 primary outcome measures in Studies 1, 2 and 3 were the erectile function domain of the International Index of Erectile Function (IIEF) and Questions 2 and 3 from Sexual Encounter Profile (SEP). The IIEF is a 4-week recall questionnaire that was administered at baseline and at 4-week intervals during treatment. The IIEF erectile function domain has a 30-point total score, where the higher scores reflect better erectile function. The SEP included diary-based measures of erectile function. Patients recorded information regarding each sexual attempt made throughout the trial. Question 2 of the SEP asks "Were you able to insert your penis into your partners vagina?" Question 3 of the SEP asks "Did your erection last long enough for you to have successful intercourse?"

In Study 4, the primary efficacy variable was the per-subject proportion of sexual attempts that had an erectogenic effect within approximately 15 minutes following dosing, where an erectogenic effect was defined as an erection sufficient for vaginal penetration and that enabled satisfactory completion of sexual intercourse.

Results are shown from the three, Phase 3, randomized, double-blind, placebo-controlled, parallel studies, one in the general ED population (Study 1), another in the diabetic population with ED (Study 2), and another in the radical prostatectomy population (Study 3).

Results in the General ED Population (Study 1):

STENDRA was evaluated in 646 men with ED of various etiologies (organic, psychogenic, mixed), in a randomized, double-blinded, parallel, placebo controlled fixed dose trial of 3 months duration. The mean age was 55.7 years (range 23 to 88 years). The population was 85.6% White, 13.2% Black, 0.9% Asian, and 0.3% of other races. The mean duration of ED was approximately 6.5 years. STENDRA at doses of 50 mg, 100 mg, and 200 mg demonstrated statistically significant improvement in all 3 primary efficacy variables relative to placebo (see Table 7).

Table 7: Mean Change From Baseline for Primary Efficacy Variables in General ED Population (Study 1)
 | Placebo (N=155) | STENDRA 50 mg (N=154) | STENDRA 100 mg (N=157) | STENDRA 200 mg (N=156)
IIEF EF Domain Score
Endpoint | 15.3 | 18.1 | 20.9 | 22.2
Change from baseline† | 2.9 | 5.4 | 8.3 | 9.5
p-value* |  | 0.0014 | <0.0001 | <0.0001
Vaginal Penetration (SEP2)
Endpoint | 53.8% | 64.3% | 73.9% | 77.3%
Change from baseline | 7.1% | 18.2% | 27.2% | 29.8%
p-value* | - | 0.0009 | <0.0001 | <0.0001
Successful Intercourse (SEP3)
Endpoint | 27.0% | 41.3% | 57.1% | 57.0%
Change from baseline | 14.1% | 27.8% | 43.4% | 44.2%
p-value* | - | 0.0002 | <0.0001 | <0.0001
† least-squares estimate from ANCOVA model * comparison to placebo for change from baseline

Results in the ED Population with Diabetes Mellitus (Study 2)

STENDRA was evaluated in ED patients (n=390) with type 1 or type 2 diabetes mellitus in a randomized, double-blind, parallel, placebo-controlled fixed dose trial of 3 months in duration. The mean age was 58 years (range 30 to 78 years). The population was 80.5% White, 17.2% Black, 1.5% Asian, and 0.8% of other races. The mean duration of ED was approximately 6 years. In this trial, STENDRA at doses of 100 mg and 200 mg demonstrated statistically significant improvement in all 3 primary efficacy variables as measured by the erectile function domain of the IIEF questionnaire; SEP2 and SEP3 (see Table 8).

Table 8: Mean Change From Baseline for Primary Efficacy Variables in ED Population with Diabetes Mellitus (Study 2)
 | Placebo (N=127) | STENDRA 100 mg (N=126) | STENDRA 200 mg (N=126)
IIEF EF Domain Score
Endpoint | 13.2 | 15.8 | 17.3
Change from baseline† | 1.8 | 4.5 | 5.4
p-value* | - | 0.0017 | <0.0001
Vaginal Penetration (SEP2)
Endpoint | 42.0% | 54.0% | 63.5%
Change from baseline | 7.5% | 21.5% | 25.9%
p-value* | - | 0.0004 | <0.0001
Successful Intercourse (SEP3)
Endpoint | 20.5% | 34.4% | 40.0%
Change from baseline | 13.6% | 28.7% | 34.0%
p-value* | - | <0.0001 | <0.0001
† least-squares estimate from ANCOVA model * comparison to placebo for change from baseline

Results in the ED Population following Radical Prostatectomy (Study 3)

The efficacy of STENDRA was evaluated in Study 3 (NCT00895011), a randomized, double-blind, parallel, placebo-controlled fixed dose trial of 3 months in duration. For study inclusion, patients had to have ED following bilateral, nerve-sparing radical prostatectomy. Patients received STENDRA 100 mg or 200 mg once daily. A total of 286 patients were included in the efficacy population: mean age 58.4 years (range 40 to 70 years), 81.5% White, 18.1% Black and 0.3% of other races. Treatment with STENDRA at doses of 100 mg and 200 mg demonstrated statistically significant improvement in all 3 primary efficacy variables relative to placebo (see Table 9).

Table 9: Mean Change From Baseline for Primary Efficacy Variables in ED Population Following Radical Prostatectomy (Study 3)
 | Placebo; (N=96) | STENDRA 100 mg; (N=94) | STENDRA 200 mg; (N=96)
IIEF EF Domain Score
Endpoint | 9.3 | 12.6 | 14.7
Change from baseline† | 1.2 | 4.7 | 6.2
p-value* | - | 0.0001 | <0.0001
Vaginal Penetration (SEP2)
Endpoint | 19.7% | 32.5% | 40.8%
Change from baseline† | 7.5% | 22.3% | 27.7%
p-value* | - | 0.0003 | <0.0001
Successful Intercourse (SEP3)
Endpoint | 8.9% | 23.4% | 26.4%
Change from baseline† | 13.9% | 28.0% | 29.4%
p-value* | - | 0.0004 | <0.0001
† least-squares estimates were obtained using an Analysis of Covariance (ANCOVA) model with treatment and baseline ED severity category as factors and baseline value as a covariate. * comparison to placebo for change from baseline

Time to Onset of Effect (Study 4)

STENDRA was evaluated in 440 subjects with ED including diabetics (16.4%) and subjects with severe ED (41.4%) in a randomized double-blind, parallel, placebo-controlled study of 2 months duration. The mean age was 58.2 years (range 24 to 86 years). The population was 75.7% White, 21.4% Black, 1.6% Asian, and 1.4% of other races. Subjects were encouraged to attempt intercourse approximately 15 minutes after dosing and used a stopwatch for measurement of time to onset of effect, defined as the time to the first occurrence of an erection sufficient for sexual intercourse.

STENDRA 100 mg and 200 mg demonstrated statistically significant improvements relative to placebo in the primary efficacy variable, percentage of all attempts resulting in an erection sufficient for penetration at approximately 15 minutes after dosing followed by successful intercourse (SEP3) (see Table 10).

Table 10: Percentage of All Attempts Resulting in an Erection Sufficient for Penetration at Approximately 15 minutes After Dosing Followed by Successful Intercourse (SEP3) During the 8-Week Treatment Period in the Time to Onset of Effect (Study 4)
 | Placebo (N=136) | STENDRA 100 mg (N=139) | STENDRA 200 mg (N=139)
Percentage of Successful Intercourse (SEP3)
Mean | 14.9 | 25.9 | 29.1
Median | 0.0 | 11.1 | 13.3
p-value* | - | 0.001 | <0.001

*comparison to placebo using rank-ANCOVA model.

16 HOW SUPPLIED/STORAGE AND HANDLING

STENDRA (avanafil) is supplied as oval, pale yellow tablets containing 50 mg, 100 mg, or 200 mg avanafil debossed with dosage strengths.

 | 50 mg | 100 mg | 200 mg
Bottle of 30 | NDC 72384-751-30 | NDC 72384-752-30 | NDC 72384-753-30

Recommended Storage: Store at 20-25°C (68-77°F); excursions permitted, 15-30°C (59-86°F) [see USP Controlled Room Temperature].

Protect from light.

17 PATIENT COUNSELING INFORMATION

Advise the patient to read the FDA-approved patient labeling (Patient Information).

17.1 Nitrates

Physicians should discuss with patients the contraindication of STENDRA with regular and/or intermittent use of organic nitrates. Patients should be counseled that concomitant use of STENDRA with nitrates could cause blood pressure to suddenly drop to an unsafe level, resulting in dizziness, syncope, or even heart attack or stroke.

Physicians should discuss with patients the appropriate action in the event that they experience anginal chest pain requiring nitroglycerin following intake of STENDRA. In such a patient, who has taken STENDRA, where nitrate administration is deemed medically necessary in a life-threatening situation, at least 12 hours should elapse after the last dose of STENDRA before nitrate administration is considered. In such circumstances, nitrates should still only be administered under close medical supervision with appropriate hemodynamic monitoring. Patients who experience anginal chest pain after taking STENDRA should seek immediate medical attention [see Contraindications (4.1) and Warnings and Precautions (5.1)].

17.2 Cardiovascular Considerations

Physicians should discuss with patients the potential cardiac risk of sexual activity in patients with preexisting cardiovascular risk factors. Patients who experience symptoms upon initiation of sexual activity should be advised to refrain from further sexual activity and should seek immediate medical attention [see Warnings and Precautions (5.1)].

17.3 Concomitant Use with Drugs Which Lower Blood Pressure

Physicians should advise patients of the potential for STENDRA to augment the blood pressure-lowering effect of alpha-blockers and other antihypertensive medications [see Warnings and Precautions (5.6), Drug Interactions (7.1), and Clinical Pharmacology (12.2)].

17.4 Potential for Drug Interactions

Patients should be advised to contact the prescribing physician if new medications that may interact with STENDRA are prescribed by another healthcare provider.

17.5 Priapism

There have been rare reports of prolonged erections greater than 4 hours and priapism (painful erections greater than 6 hours in duration) for this class of compounds. Priapism, if not treated promptly, can result in irreversible damage to the erectile tissue. Physicians should advise patients who have an erection lasting greater than 4 hours, whether painful or not, to seek emergency medical attention.

17.6 Vision

Physicians should advise patients to stop use of all PDE5 inhibitors, including STENDRA, and seek medical attention in the event of a sudden loss of vision in one or both eyes. Such an event may be a sign of non-arteritic anterior ischemic optic neuropathy (NAION), a cause of decreased vision including permanent loss of vision that has been reported rarely in temporal association with the use of PDE5 inhibitors. Physicians should discuss with patients the increased risk of NAION in individuals who have already experienced NAION in one eye. Physicians should also discuss with patients the increased risk of NAION among the general population in patients with a “crowded” optic disc, although evidence is insufficient to support screening of prospective users of PDE5 inhibitor, including STENDRA, for these uncommon conditions [see Warnings and Precautions (5.4) and Adverse Reactions (6.2)].

17.7 Sudden Hearing Loss

Physicians should advise patients to stop taking PDE5 inhibitors, including STENDRA, and seek prompt medical attention in the event of sudden decrease or loss of hearing. Use of PDE5 inhibitors has been associated with sudden decrease or loss of hearing, which may be accompanied by tinnitus and dizziness. It is not possible to determine whether these events are related directly to the use of PDE5 inhibitors or to other factors [see Adverse Reactions (6)].

17.8 Alcohol

Patients should be made aware that both alcohol and PDE5 inhibitors including STENDRA act as mild vasodilators. When mild vasodilators are taken in combination, blood pressure-lowering effects of each individual compound may be increased. Therefore, physicians should inform patients that substantial consumption of alcohol (e.g., greater than 3 units) in combination with STENDRA can increase the potential for orthostatic signs and symptoms, including increase in heart rate, decrease in standing blood pressure, dizziness, and headache [see Warnings and Precautions (5.7) and Clinical Pharmacology (12.2)].

17.9 Sexually Transmitted Disease

The use of STENDRA offers no protection against sexually transmitted diseases. Counseling of patients about the protective measures necessary to guard against sexually transmitted diseases, including Human Immunodeficiency Virus (HIV) should be considered.

17.10 Recommended Administration

Physicians should discuss with patients the appropriate use of STENDRA and its anticipated benefits. It should be explained that sexual stimulation is required for an erection to occur after taking STENDRA. Patients should be counseled regarding the dosing of STENDRA. Inform patients that the recommended starting dose of STENDRA is 100 mg, taken as early as approximately 15 minutes before initiation of sexual activity. Based on efficacy and tolerability, the dose may be increased to 200 mg taken as early as approximately 15 minutes before sexual activity, or decreased to 50 mg taken approximately 30 minutes before sexual activity. The lowest dose that provides benefit should be used. Patients should be advised to contact their healthcare provider for dose modification.

17.11 Guanylate Cyclase (GC) Stimulators

Physicians should discuss with patients the contraindication of STENDRA with use of guanylate cyclase stimulators such as riociguat or vericiguat [see Contraindications (4.3)].

Manufactured for: Metuchen Pharmaceuticals, LLC, Freehold, NJ 07728
By: Sanofi Winthrope Industrie, Ambares, France

© Metuchen Pharmaceuticals, LLC. All rights reserved.
US Patent Number: 6,656,935 and 7,501,409
STENDRA is a registered U.S. trademark of Metuchen Pharmaceuticals, LLC.
375F101

Patient Information

STENDRA® (sten-druh)

(avanafil)

tablets, for oral use

What is the most important information I should know about STENDRA?

STENDRA can cause your blood pressure to drop suddenly to an unsafe level if it is taken with certain other

medicines. Do not take STENDRA if you take any medicines called nitrates. Nitrates are used to treat chest pain

(angina). A sudden drop in blood pressure can cause you to feel dizzy, faint, or have a heart attack or stroke.

Do not take STENDRA if you take medicines called guanylate cyclase stimulators which include:

• Riociguat and vericiguat, medicines that treat pulmonary arterial hypertension and chronic-thromboembolicpulmonary hypertension.

Ask your healthcare provider or pharmacist if any of your medicines are nitrates or guanylate cyclase stimulators.

Tell all your healthcare providers that you take STENDRA. If you need emergency medical care for a heartproblem, it will be important for your healthcare provider to know when you last took STENDRA.

Stop sexual activity and get medical help right away if you get symptoms such as chest pain, dizziness, or nausea

during sex. Sexual activity can put an extra strain on your heart, especially if your heart is already weak from a heart

attack or heart disease.

What is STENDRA?

STENDRA is a prescription medicine used to treat erectile dysfunction (ED) in adult men.

STENDRA is not for use in women or children.

It is not known if STENDRA is safe and effective in women or children under 18 years of age.

Do not take STENDRA if you:

• take medicines called nitrates.

• use street drugs called “poppers” such as amyl nitrite and butyl nitrite.

• are allergic to avanafil or any of the ingredients in STENDRA. See the end of this leaflet for a complete list ofingredients in STENDRA.

• take any medicines called guanylate cyclase stimulators.

Before you take STENDRA, tell your healthcare provider about all of your medical conditions, including if you:

• have or have had heart problems such as a heart attack, irregular heartbeat, angina, or heart failure.

• have had heart surgery within the last 6 months.

• have had a stroke.

• have low blood pressure, or high blood pressure that is not controlled.

• have a deformed penis shape.

• have had an erection that lasted for more than 4 hours.

• have problems with your blood cells such as sickle cell anemia, multiple myeloma, or leukemia.

• have retinitis pigmentosa, a rare genetic (runs in families) eye disease.

• have ever had severe vision loss, including an eye problem called non-arteritic anterior ischemic optic neuropathy(NAION).

• have had a sudden decrease or loss of hearing.

• have bleeding problems.

• have or have had stomach ulcers.

• have liver problems.

• have kidney problems or are having kidney dialysis.

Tell your healthcare provider about all the medicines you take, including prescription and over-the-counter

medicines, vitamins, and herbal supplements.

STENDRA may affect the way other medicines work, and other medicines may affect the way STENDRA works

causing side effects. Especially tell your healthcare provider if you take any of the following:

• medicines called nitrates (see What is the most important information I should know about STENDRA?)

• medicines called guanylate cyclase stimulators, such a riociguat or vericiguat (see What is the most importantinformation I should know about STENDRA?)

• medicines called HIV protease inhibitors.

• some types of oral antifungal medicines, such as ketoconazole, and itraconozale.

• some types of antibiotics, such as clarithromycin, telithromycin, or erythromycin.

• medicines called alpha blockers. These include terazosin, tamsulosin HCl, doxazosin, prazosin HCl, alfuzosin HCl,

dutasteride and tamsulosin HCl, or silodosin. Alpha-blockers are sometimes prescribed for prostate problems or

high blood pressure. In some patients, the use of STENDRA with alpha-blockers can lead to a drop in blood

pressure or to fainting.

• other medicines that treat high blood pressure.

• other medicines or treatments for ED.

Ask your healthcare provider or pharmacist for a list of these medicines, if you are not sure.

Know the medicines you take. Keep a list of them to show to your healthcare provider and pharmacist when you get a

new medicine.

How should I take STENDRA?

• Take STENDRA exactly as your healthcare provider tells you to take it.

• Your healthcare provider will tell you how much STENDRA to take and when to take it.

• Take STENDRA 100 mg or 200 mg as early as 15 minutes before sexual activity or

• Take STENDRA 50 mg as early as 30 minutes before sexual activity.• Do not take STENDRA more than 1 time a day.

• Some form of sexual stimulation is needed for an erection to happen after taking STENDRA.

• Your healthcare provider may change your dose if needed.

• You should take the lowest dose of STENDRA that works for you. You and your healthcare provider should decide

about the lowest dose of STENDRA that works for you.

• STENDRA may be taken with or without food.

• If you take too much STENDRA, call your healthcare provider or go to the nearest hospital emergency room rightaway.

What should I avoid while taking STENDRA?

• Do not drink too much alcohol when taking STENDRA (for example, 3 glasses of wine, or 3 shots of whiskey).

Drinking too much alcohol when taking STENDRA can increase your chances of increasing your heart rate,

lowering your blood pressure, dizziness or getting a headache.

What are the possible side effects of STENDRA?

STENDRA can cause serious side effects, including:

• See “What is the most important information I should know about STENDRA?”

• an erection that will not go away (priapism). If you have an erection that lasts more than 4 hours, get medical

help right away. If it is not treated right away, priapism can permanently damage your penis.

• sudden vision loss in 1 or both eyes. Sudden vision loss in 1 or both eyes can be a sign of a serious eye

problem called non-arteritic anterior ischemic optic neuropathy (NAION). It is uncertain whether PDE5 inhibitors

such as STENDRA, directly cause vision loss. Stop taking STENDRA and call your healthcare provider right away

if you have sudden vision loss in 1 or both eyes.

• sudden hearing decrease or hearing loss. Some people may also have ringing in their ears (tinnitus) or

dizziness.

The most common side effects of STENDRA are:

• headache

• flushing

• stuffy or runny nose

• sore throat

• back pain

These are not all of the possible side effects of STENDRA.

Call your doctor for medical advice about side effects. You may report side effects to FDA at 1-800-FDA-1088.

How should I store STENDRA?

• Store STENDRA at room temperature between 68°F to 77°F (20°C to 25°C).

• Keep STENDRA out of the light.

Keep STENDRA and all medicines out of the reach of children

General information about the safe and effective use of STENDRA.

Medicines are sometimes prescribed for purposes other than those listed in a Patient Information leaflet. Do not use

STENDRA for a condition for which it was not prescribed. Do not give STENDRA to other people, even if they have

the same symptoms that you have. It may harm them. You can ask your healthcare provider or pharmacist for

information about STENDRA that is written for health professionals.

What are the ingredients in STENDRA?

Active ingredient: avanafil. Inactive ingredients: mannitol, fumaric acid, hydroxypropylcellulose, low substituted

hydroxypropylcellulose, calcium carbonate, magnesium stearate, and ferric oxide yellow.

Manufactured for: Metuchen Pharmaceuticals, LLC, Freehold, NJ 07728By: Sanofi Winthrope Industrie, Ambares, France;

© Metuchen Pharmaceuticals, LLC. All rights reserved.

US Patent Number: 6,656,935 and 7,501,409

STENDRA is a registered U.S. trademark of Metuchen Pharmaceuticals, LLC.

375P100

For more information, go to www.STENDRA.com or call 1-844-458-4887

This Patient Information has been approved by the U.S. Food and Drug Administration Revised: October/2022

PACKAGE LABEL

PRINCIPAL DISPLAY PANEL
NDC 72384-751-30
STENDRA
(avanafil) tablets
50 mg
Rx Only
30 Tablets

PACKAGE LABEL

PRINCIPAL DISPLAY PANEL
NDC 72384-752-30
STENDRA
(avanafil) tablets
100 mg
Rx Only
30 Tablets

PACKAGE LABEL

PRINCIPAL DISPLAY PANEL
NDC 72384-753-30
STENDRA
(avanafil) tablets
200 mg
Rx Only
30 Tablets